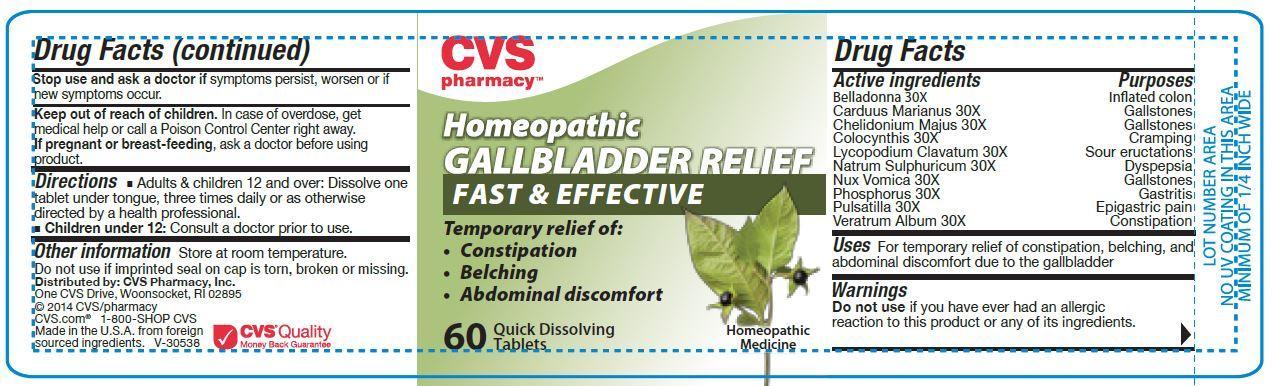 DRUG LABEL: Gallbladder Relief
NDC: 59779-858 | Form: TABLET
Manufacturer: WOONSOCKET PRESCR CTR INC
Category: homeopathic | Type: HUMAN OTC DRUG LABEL
Date: 20141111

ACTIVE INGREDIENTS: ATROPA BELLADONNA 30 [hp_X]/60 1; MILK THISTLE 30 [hp_X]/60 1; CHELIDONIUM MAJUS 30 [hp_X]/60 1; CITRULLUS COLOCYNTHIS FRUIT PULP 30 [hp_X]/60 1; LYCOPODIUM CLAVATUM SPORE 30 [hp_X]/60 1; SODIUM SULFATE 30 [hp_X]/60 1; STRYCHNOS NUX-VOMICA SEED 30 [hp_X]/60 1; PHOSPHORUS 30 [hp_X]/60 1; PULSATILLA VULGARIS 30 [hp_X]/60 1; VERATRUM ALBUM ROOT 30 [hp_X]/60 1
INACTIVE INGREDIENTS: LACTOSE; MAGNESIUM STEARATE; MANNITOL; CELLULOSE, MICROCRYSTALLINE

Active Ingredients Purposes

Belladonna 30X ......................................... Inflated colon

Carduus Marianus 30X ................................... Gallstones

Chelidonium Majus 30X .................................. Gallstones

Colocynthis 30X .............................................. Cramping

Lycopodium Clavatum 30X ................... Sour Eructations

Natrum Sulphuricum 30X ............................... Dyspepsia

Nux Vomica 30X ............................................ Gallstones

Phosphorus 30X ................................................ Gastritis

Pulsatilla 30X ........................................... Epigastric Pain

Veratrum Album 30X .................................. Constipation

Uses

For temporary relief of constipation, belching, and abdominal discomfort due to the gallbladder.

Keep out of reach of children. In case of overdose, get medical help or call a Poison Control Center right away.

INDICATIONS AND USAGE

CVS

NEW!

Homeopathic GALLBLADDER RELIEF

FAST & EFFECTIVE

Temporary relief of:

- Constipation
- Belching
- Abdominal discomfort

60 Quick Dissolving Tablets

Homeopathic Medicine

Directions

Adults & children 12 times and over: Dissolve one tablet under tongue, three times daily or as otherwise directed by a health professional.

Children under 12: Consult a doctor prior to use.

Warnings

Do not use if you have ever had an allergic reaction to this product or any of its ingredients.

Stop use and ask a doctor if symptoms persist, worsen or if new symptoms occur.

If pregnant or breast-feeding, ask a doctor before using product.

Inactive Ingredients

Advantol® 300, lactose, magnesium stearate, mannitol, microcrystalline cellulose.